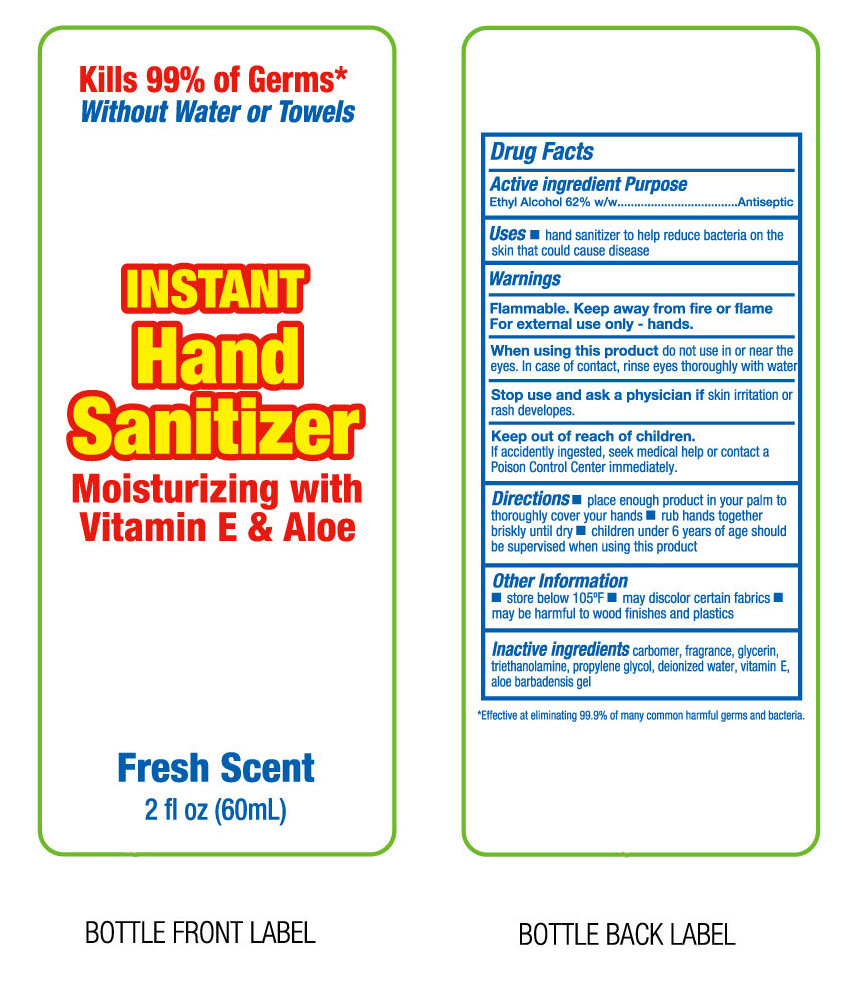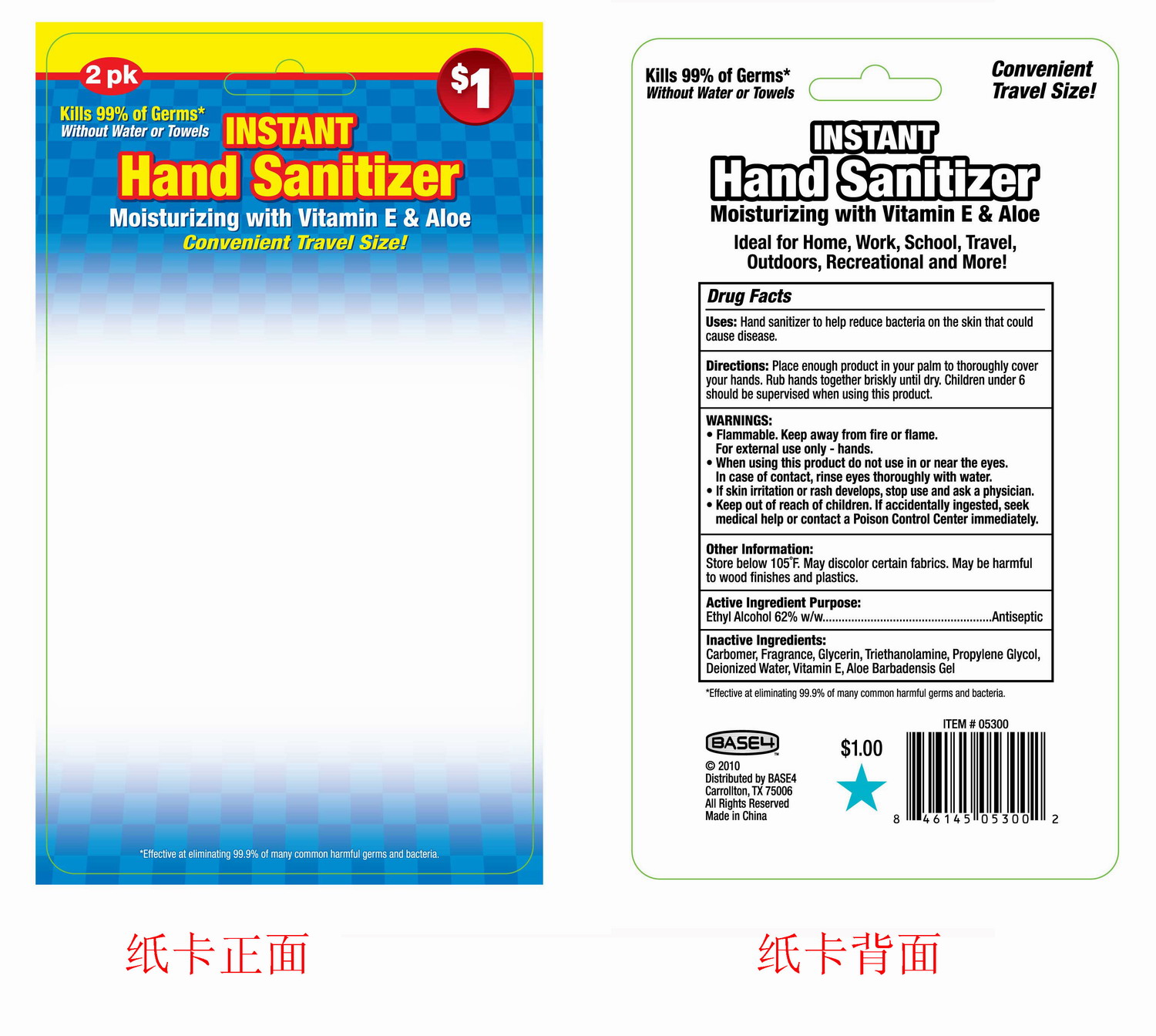 DRUG LABEL: Instant Hand Sanitizer
NDC: 25225-015 | Form: LIQUID
Manufacturer: Unique Holding Group Inc
Category: otc | Type: HUMAN OTC DRUG LABEL
Date: 20100505

ACTIVE INGREDIENTS: ALCOHOL 62 g/100 g
INACTIVE INGREDIENTS: Water 35.6 g/100 g; Propylene Glycol  0.5 g/100 g; Glycerin 1 g/100 g; ALOE VERA LEAF 0.01 g/100 g; CARBOMER HOMOPOLYMER TYPE C 0.33 g/100 g; ALPHA-TOCOPHEROL 0.01 g/100 g; TROLAMINE 0.35 g/100 g

Drug Facts

Active Ingredient Purpose

Ethyl Alcohol 62% w/w Antiseptic

Uses:

Hand sanitizer to help decrease bacteria on the skin that could cause diseases

Warnings:

Flammable. Keep away from fore or flame.

For external use only-hands.

When using this product, do not use in or near the eyes. In case of contact, rinse eyes thoroughly with water.

Stop use and ask a physician if irritation or skin rash develops.

Keep out of reach of children

if accidentally ingested, seek medical help or contact a Poison Control Center immediately.

Directions

- Place enough product in your palm to thoroughly cover your hands
- rub hands briskly together until dry
- children under 6 years of age should be supervised when using this product

Other Information

- Store below 105F
- May discolor certain fabrics.
- Maybe harmful to wood finishes and plastics

Inactive Ingredients:

carbomer, fragrance, glycerin, triethanolamine, propylene glycol, deionized water, aloe barbadensis gel

PACKAGE LABEL

th

PACKAGE LABEL

card